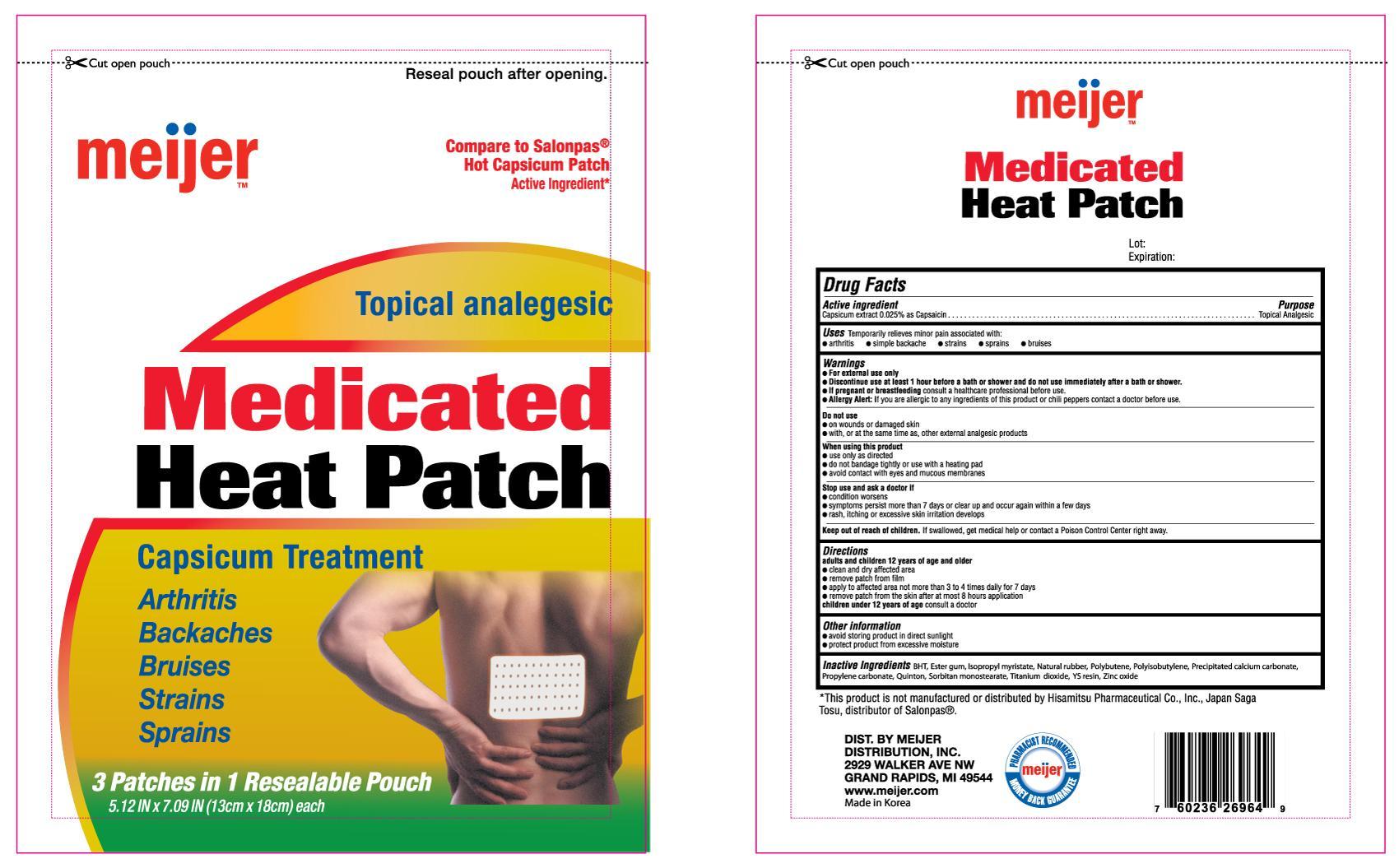 DRUG LABEL: Meijer Medicated Heat
NDC: 41250-269 | Form: PATCH
Manufacturer: Meijer
Category: otc | Type: HUMAN OTC DRUG LABEL
Date: 20130630

ACTIVE INGREDIENTS: CAPSICUM 0.6 mg/1 1
INACTIVE INGREDIENTS: BUTYLATED HYDROXYTOLUENE; ISOPROPYL MYRISTATE; NATURAL LATEX RUBBER; PROPYLENE CARBONATE; SORBITAN MONOSTEARATE; TITANIUM DIOXIDE; ZINC PEROXIDE

Drug Facts

Active ingredient Purpose

Capsicum extract 0.025% as Capsaicin..................................Topical Analgesic

PURPOSE

Uses Temporarily relieves minor pain associated with:

- arthritis
- simple backache
- strains
- sprains
- bruises

Warnings

- For external use only
- Discontinue use at least 1 hour before a bath or shower and do not use immediately after a bath or shower.
- Allergy Alert: If you are allergic to any ingredients of this product or chili peppers contact a doctor before use

Do not use

- on wounds or damaged skin
- with, or at the same time as other external analgesic products

When using this product

- use only as directed
- do not bandage tightly or use with a heating pad
- avoid contact with eyes and mucous membranes

Stop use and ask a doctor if

- condition worsens
- symptoms persist more than 7 days or clear up and occur again within a few days
- rash, itching or excessive skin irritation develops

PREGNANCY OR BREAST FEEDING

If pregnant or breastfeeding consult a healthcare professional before use.

Keep out of reach of children. If swollen, get medical help or contact a Poison Control Center right away.

Directions

- adults and children 12 years of age and older:
- clean and dry affected area
- remove patch from film
- apply to affected area not more than 3 to 4 times daily for 7 days
- remove patch from the skin after at most 8 hours application
- children under 12 years of age: consult a doctor

Other information

- avoid storing product in direct sunlight
- protect product from excessive moisture

INACTIVE INGREDIENT

Inactive Ingredients BHT, Ester gum, Isopropyl myristate, Natural rubber, Polybutene, Polyisobutylene, Precipitated calcium carbonate, Propylene carbonate, Quinton, Sorbitan monostearate, Titanium dioxide, YS resin, Zinc oxide

DOSAGE AND ADMINISTRATION

Distributed By:

Meijer Distribution Inc.

2929 Walker Ave

Grand Rapids, MI 49544

Made in Korea